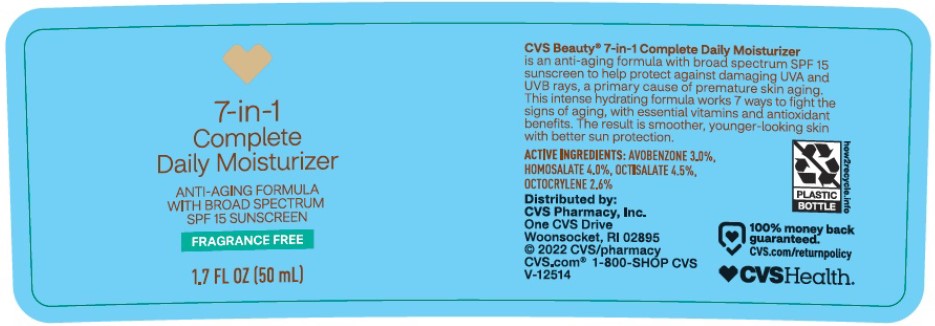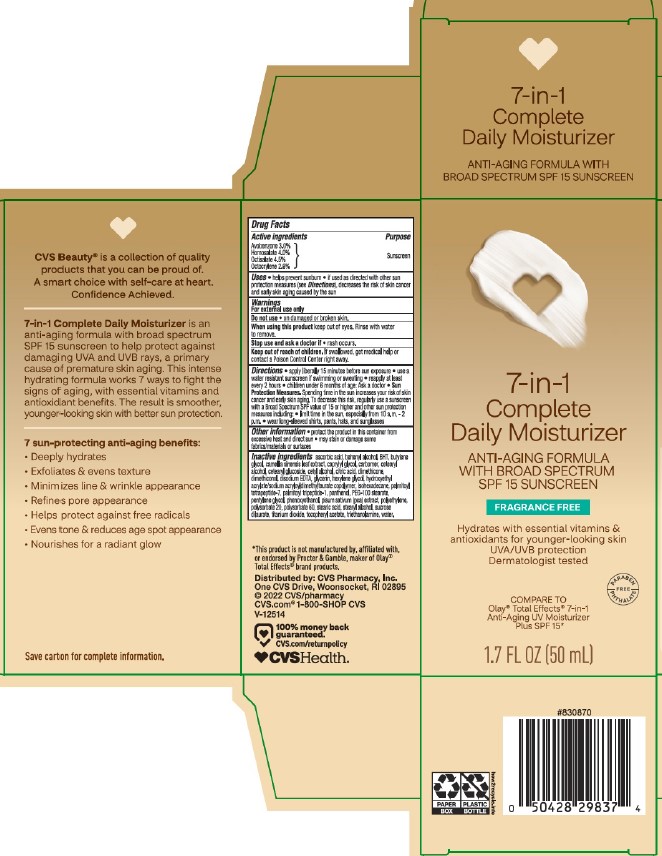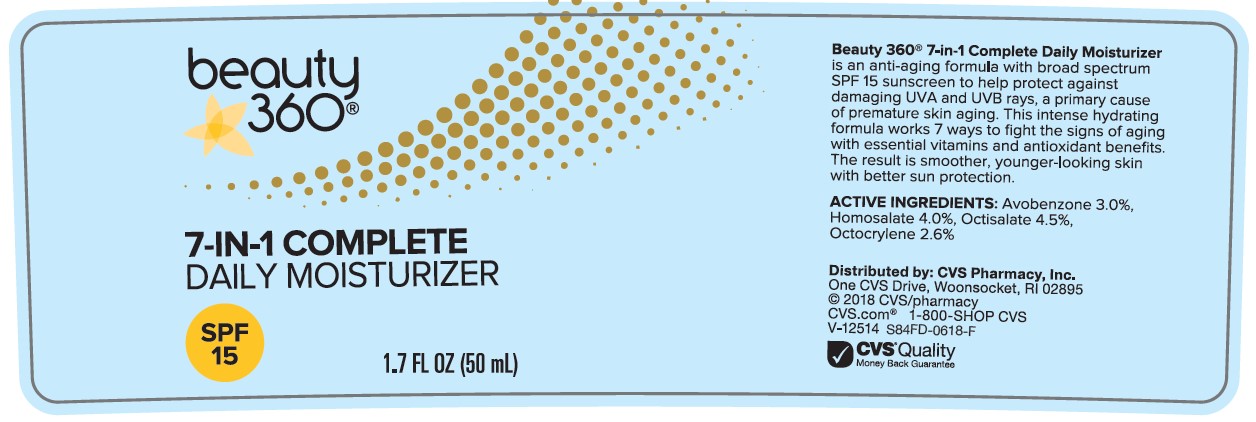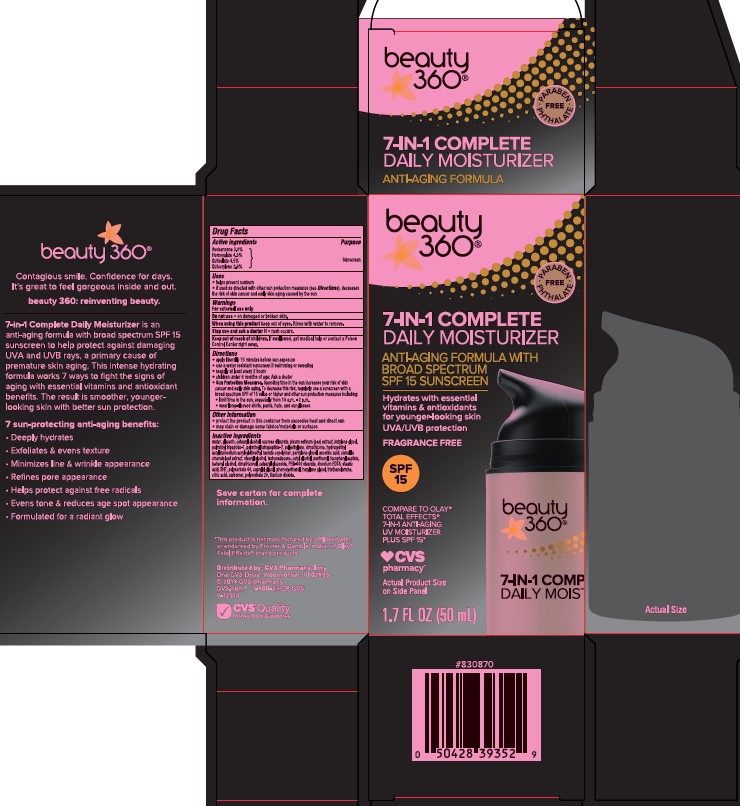 DRUG LABEL: CVS Beauty 360 7-in-1 Complete Daily Moisturizer Anti-Aging Formula with Broad Spectrum SPF 15 Sunscreen
NDC: 51316-049 | Form: LOTION
Manufacturer: CVS Pharmacy
Category: otc | Type: HUMAN OTC DRUG LABEL
Date: 20240716

ACTIVE INGREDIENTS: AVOBENZONE 30 mg/1 mL; HOMOSALATE 40 mg/1 mL; OCTOCRYLENE 26 mg/1 mL; OCTISALATE 45 mg/1 mL
INACTIVE INGREDIENTS: WATER; HIGH DENSITY POLYETHYLENE; CETOSTEARYL ALCOHOL; DIMETHICONE; PEG-100 STEARATE; STEARYL ALCOHOL; DOCOSANOL; TITANIUM DIOXIDE; DIMETHICONOL (100000 CST); PANTHENOL; GLYCERIN; ISOHEXADECANE; SUCROSE DILAURATE; CETEARYL GLUCOSIDE; POLYSORBATE 20; CETYL ALCOHOL; STEARIC ACID; BUTYLENE GLYCOL; HYDROXYETHYL ACRYLATE/SODIUM ACRYLOYLDIMETHYL TAURATE COPOLYMER (45000 MPA.S AT 1%); BUTYLATED HYDROXYTOLUENE; PENTYLENE GLYCOL; PEA; ANHYDROUS CITRIC ACID; EDETATE DISODIUM; ASCORBIC ACID; PALMITOYL TETRAPEPTIDE-7; PALMITOYL TRIPEPTIDE-1; .ALPHA.-TOCOPHEROL ACETATE; POLYSORBATE 60; TROLAMINE; CAMELLIA SINENSIS FLOWER; HEXYLENE GLYCOL; PHENOXYETHANOL; CAPRYLYL GLYCOL

CVS Beauty 360 7-in-1 Complete Daily Moisturizer Anti-Aging Formula with Broad Spectrum SPF 15 Sunscreen

Active ingredients

Avobenzone 3.0%, Homosalate 4.0%, Octisalate 4.5%, Octocrylene 2.6%

Purpose

Sunscreen

Uses

- helps prevent sunburn
- if used as directed with other sun protection measures (see Directions), decreases the risk of skin cancer and early skin aging caused by the sun

Warnings

For external use only

Do not use

on damaged or broken skin

When using this product

keep out of eyes. Rinse with water to remove.

Stop use and ask a doctor

if rash occurs.

Keep out of reach of children.

If product is swallowed, get medical help or contact a Poison Control Center right away.

Directions

• apply liberally 15 minutes before sun exposure

•use a water resistant sunscreen if swimming or sweating
• reapply at least every 2 hours
• Sun Protection Measures. Spending time in the sun increases your risk of skin cancer and early skin aging. To decrease this risk, regularly use a sunscreen with a Broad Spectrum SPF value of 15 or higher and other sun protection measures including:
• limit time in the sun, especially from 10 a.m. - 2 p.m.
• wear long-sleeved shirts, pants, hats, and sunglasses

• children under 6 months: Ask a doctor

Other information

• protect the product in this container from excessive heat and direct sun
• may stain or damage some fabrics, materials or surfaces

Inactive ingredients

WATER, GLYCERIN, CETEARYL ALCOHOL, SUCROSE DILAURATE, PISUM SATIVUM (PEA) EXTRACT, BUTYLENE GLYCOL, PALMITOYL OLIGOPEPTIDE, PALMITOYL TETRAPEPTIDE-7, POLYETHYLENE, DIMETHICONE, HYDROXYETHYL ACRYLATE/SODIUM ACRYLOYLDIMETHYL TAURATE COPOLYMER, PENTYLENE GLYCOL, ASCORBIC ACID, CAMELLIA SINENSIS LEAF EXTRACT, STEARYL ALCOHOL, ISOHEXADECANE, CETYL ALCOHOL, PANTHENOL, TOCOPHERYL ACETATE, BEHENYL ALCOHOL, DIMETHICONOL, CETEARYL GLUCOSIDE, PEG-100 STEARATE, DISODIUM EDTA, STEARIC ACID, BHT, POLYSORBATE 60, CAPRYLYL GLYCOL, PHENOXYETHANOL, HEXYLENE GLYCOL, TRIETHANOLAMINE, CITRIC ACID, CARBOMER, POLYSORBATE-20, TITANIUM DIOXIDE.